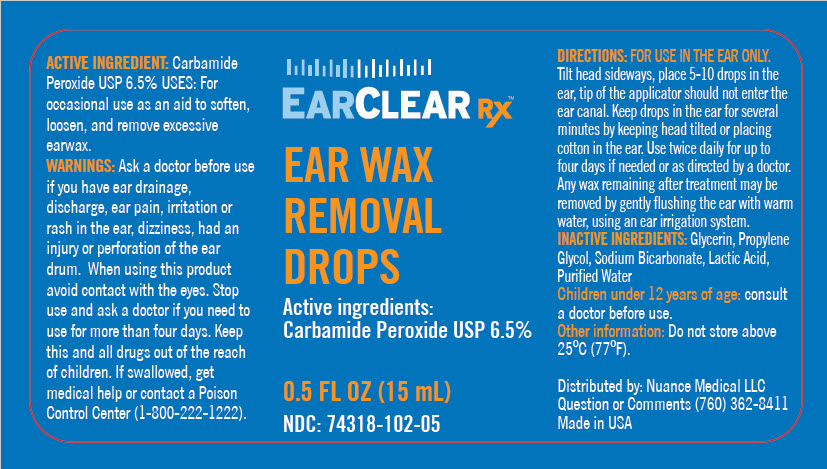 DRUG LABEL: EarClearRx
NDC: 74318-102 | Form: SOLUTION/ DROPS
Manufacturer: Nuance Medical, LLC
Category: otc | Type: HUMAN OTC DRUG LABEL
Date: 20211112

ACTIVE INGREDIENTS: CARBAMIDE PEROXIDE 65 mg/1 mL
INACTIVE INGREDIENTS: GLYCERIN; PROPYLENE GLYCOL; WATER; SODIUM BICARBONATE; LACTIC ACID, UNSPECIFIED FORM

EarClearRx™

ACTIVE INGREDIENT

Carbamide Peroxide USP 6.5%

USES

PURPOSE

For occasional use as an aid to soften, loosen, and remove excessive earwax.

WARNINGS

Ask a doctor before use if you have ear drainage, discharge, ear pain, irritation or rash in the ear, dizziness, had an injury or perforation of the ear drum. When using this product avoid contact with the eyes. Stop use and ask a doctor if you need to use for more than four days.

KEEP OUT OF REACH OF CHILDREN

Keep this and all drugs out of the reach of children. If swallowed, get medical help or contact a Poison Control Center (1-800-222-1222).

DIRECTIONS

FOR USE IN THE EAR ONLY. Tilt head sideways, place 5-10 drops in the ear, tip of the applicator should not enter the ear canal. Keep drops in the ear for several minutes by keeping head tilted or placing cotton in the ear. Use twice daily for up to four days if needed or as directed by a doctor. Any wax remaining after treatment may be removed by gently flushing the ear with warm water, using an ear irrigation system.

INACTIVE INGREDIENTS

Glycerin, Propylene Glycol, Sodium Bicarbonate, Lactic Acid, Purified Water

Children under 12 years of age: consult a doctor before use.

Other information

Do not store above 25°C (77°F).

Question or Comments

(760) 362-8411

Distributed by: Nuance Medical LLC

PRINCIPAL DISPLAY PANEL - 15 mL Bottle Label

EARCLEAR Rx™

EAR WAX
REMOVAL
DROPS

Active ingredients:
Carbamide Peroxide USP 6.5%

0.5 FL OZ (15 mL)
NDC: 74318-102-05